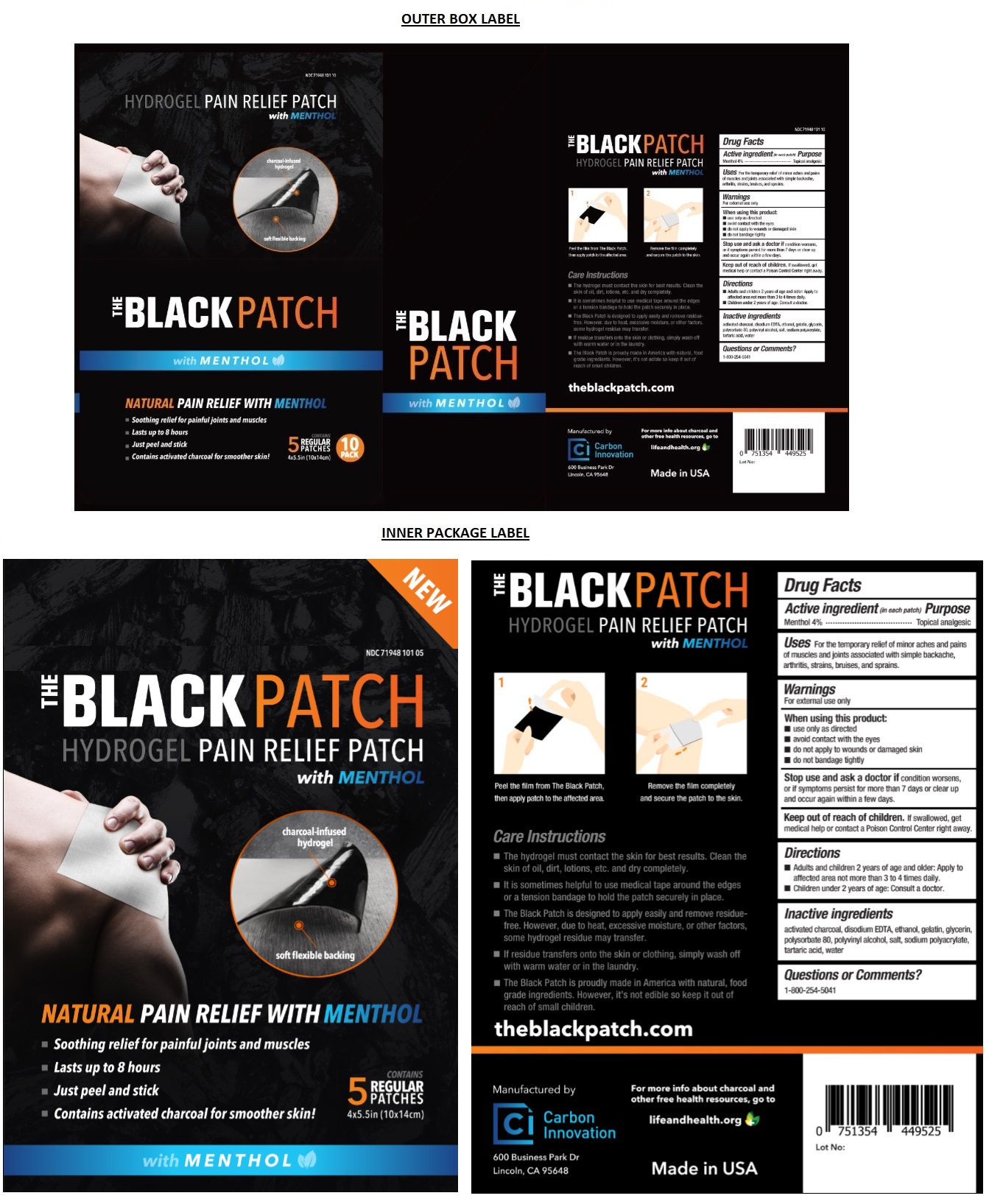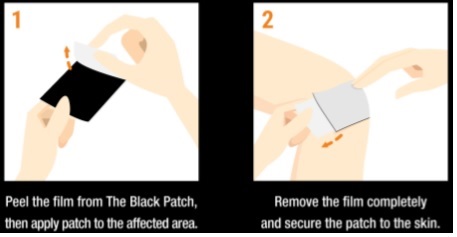 DRUG LABEL: THE BLACK Patch
NDC: 71948-101 | Form: PATCH
Manufacturer: Carbon Innovation, Inc.
Category: otc | Type: HUMAN OTC DRUG LABEL
Date: 20171222

ACTIVE INGREDIENTS: MENTHOL 4 g/100 g
INACTIVE INGREDIENTS: ACTIVATED CHARCOAL; EDETATE DISODIUM ANHYDROUS; ALCOHOL; GELATIN; GLYCERIN; POLYSORBATE 80; POLYVINYL ALCOHOL/POLYVINYL ACETATE COPOLYMER (8:1; 50000 MW); SODIUM CHLORIDE; SODIUM POLYACRYLATE (2500000 MW); TARTARIC ACID; WATER

THE BLACK PATCH

Active ingredient (in each patch)

Menthol 4%

Purpose

Topical analgesic

Uses

For the temporary relief of minor aches and pains of muscles and joints associated with simple backache, arthritis, strains, bruises, and sprains.

Warnings

For external use only

When using this product

- use only as directed
- avoid contact with the eyes
- do not apply to wounds or damaged skin
- do not bandage tightly

Stop use and ask a doctor if condition worsens, or if symptoms persist for more than 7 days or clear up and occur again within a few days.

Keep out of reach of children. If swallowed, get medical help or contact a Poison Control Center right away.

Directions

- Adults and children 2 years of age and older: Apply to affected area not more than 3 to 4 times daily.
- Children under 2 years of age: Consult a doctor.

Inactive ingredients

activated charcoal, disodium EDTA, ethanol, gelatin, glycerin, polysorbate 80, polyvinyl alcohol, salt, sodium polyacrylate, tartaric acid, water

Questions or Comments?

1-800-254-5041

HYDROGEL PAIN RELIEF PATCH with MENTHOL

- Soothing relief for painful joints and muscles
- Lasts up to 8 hours
- Just peel and stick
- Contains activated charcoal for smoother skin!

Care Instructions

- The hydrogel must contact the skin for best results. Clean the skin of oil, dirt, lotions, etc. and dry completely.
- It is sometimes helpful to use medical tape around the edges or a tension bandage to hold the patch securely in place.
- The Black Patch is designed to apply easily and remove residue-free. However, due to heat, excessive moisture, or other factors, some hydrogel residue may transfer.
- If residue transfers onto the skin or clothing, simply wash off with warm water or in the laundry.
- The Black Patch is proudly made in America with natural, food grade ingredients. However, it's not edible so keep it out of reach of small children.

Manufactured by

Carbon Innovation

600 Business Park Dr

Lincoln, CA 95648